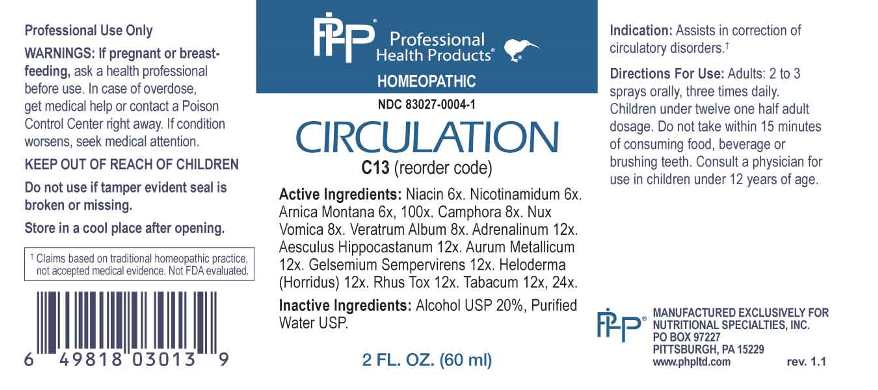 DRUG LABEL: Circulation
NDC: 83027-0004 | Form: SPRAY
Manufacturer: Nutritional Specialties, Inc.
Category: homeopathic | Type: HUMAN OTC DRUG LABEL
Date: 20240724

ACTIVE INGREDIENTS: NIACIN 6 [hp_X]/1 mL; NIACINAMIDE 6 [hp_X]/1 mL; ARNICA MONTANA WHOLE 6 [hp_X]/1 mL; CAMPHOR (NATURAL) 8 [hp_X]/1 mL; STRYCHNOS NUX-VOMICA SEED 8 [hp_X]/1 mL; VERATRUM ALBUM ROOT 8 [hp_X]/1 mL; EPINEPHRINE 12 [hp_X]/1 mL; HORSE CHESTNUT 12 [hp_X]/1 mL; GOLD 12 [hp_X]/1 mL; GELSEMIUM SEMPERVIRENS ROOT 12 [hp_X]/1 mL; HELODERMA HORRIDUM VENOM 12 [hp_X]/1 mL; TOXICODENDRON PUBESCENS LEAF 12 [hp_X]/1 mL; TOBACCO LEAF 12 [hp_X]/1 mL
INACTIVE INGREDIENTS: WATER; ALCOHOL

DRUG FACTS:

ACTIVE INGREDIENTS:

Niacin 6X, Nicotinamidum 6X, Arnica Montana 6X, 100X, Camphora 8X, Nux Vomica 8X, Veratrum Album 8X, Adrenalinum 12X, Aesculus Hippocastanum 12X, Aurum Metallicum 12X, Gelsemium Sempervirens 12X, Heloderma (Horridus) 12X, Rhus Tox 12X, Tabacum 12X, 24X.

PURPOSE:

Assists in correction of circulatory disorders.†

†Claims based on traditional homeopathic practice, not accepted medical evidence. Not FDA evaluated.

WARNINGS:

Professional Use Only

If pregnant or breast-feeding, ask a health professional before use.

In case of overdose, get medical help or contact a Poison Control Center right away.

If condition worsens, seek medical attention.

KEEP OUT OF REACH OF CHILDREN

Do not use if tamper evident seal is broken or missing.

Store in a cool place after opening

KEEP OUT OF REACH OF CHILDREN:

In case of overdose, get medical help or contact a Poison Control Center right away.

DIRECTIONS:

Adults: 2 to 3 sprays orally, three times daily. Children under twelve one half adult dosage. Do not take within 15 minutes of consuming food, beverage or brushing teeth. Consult a physician for use in children under 12 years of age.

INDICATIONS:

Assists in correction of circulatory disorders.†

†Claims based on traditional homeopathic practice, not accepted medical evidence. Not FDA evaluated.

INACTIVE INGREDIENTS:

Alcohol USP 20%, Purified Water USP.

QUESTIONS:

MANUFACTURED EXCLUSIVELY FOR

NUTRITIONAL SPECIALTIES, INC.

PO BOX 97227

PITTSBURG, PA 15229

www.phpltd.com

PACKAGE LABEL DISPLAY:

Professional

Health Products

HOMEOPATHIC

NDC 83027-0004-1

CIRCULATION

2 FL. OZ (60 ml)